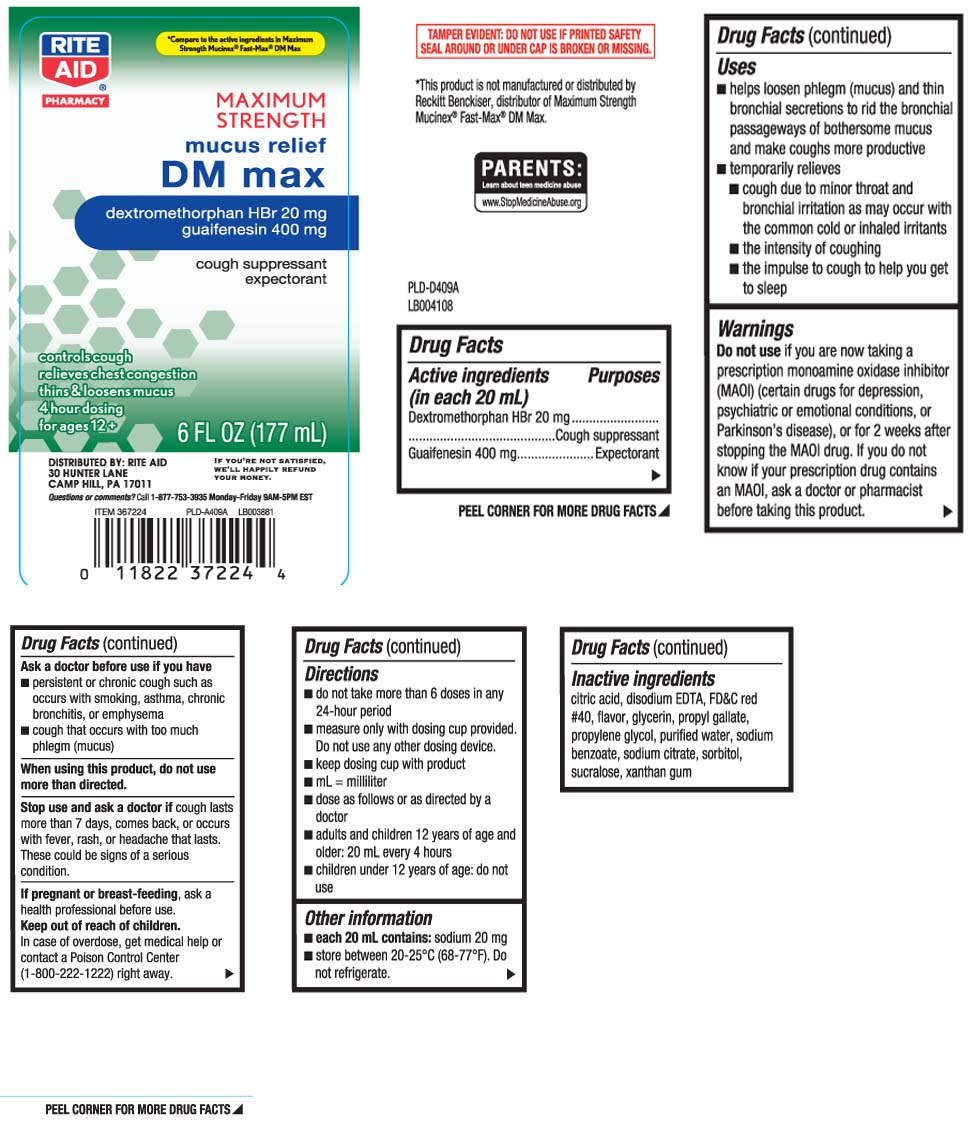 DRUG LABEL: Mucus DM
NDC: 11822-5050 | Form: LIQUID
Manufacturer: Rite Aid Corporation
Category: otc | Type: HUMAN OTC DRUG LABEL
Date: 20251120

ACTIVE INGREDIENTS: DEXTROMETHORPHAN HYDROBROMIDE 20 mg/20 mL; GUAIFENESIN 400 mg/20 mL
INACTIVE INGREDIENTS: ANHYDROUS CITRIC ACID; EDETATE DISODIUM; FD&C RED NO. 40; GLYCERIN; PROPYL GALLATE; PROPYLENE GLYCOL; WATER; SODIUM BENZOATE; TRISODIUM CITRATE DIHYDRATE; SORBITOL; SUCRALOSE; XANTHAN GUM

Drug Facts

Active ingredients (in each 20 mL)

Dextromethorphan HBr 20 mg

Guaifenesin 400 mg

Purpose

Cough suppressant

Expectorant

Uses

- helps loosen phlegm (mucus) and thin bronchial secretions to make coughs more productive
- temporarily relieves
  - cough due to minor throat and bronchial irritation as may occur with the common cold or inhaled irritants
  - the intensity of coughing
  - the impulse to cough to help you get to sleep

Warnings

Do not use

if you are now taking a prescription monoamine oxidase inhibitor (MAOI) (certain drugs for depression, psychiatric or emotional conditions, or Parkinson’s disease), or for 2 weeks after stopping the MAOI drug. If you do not know if your prescription drug contains an MAOI, ask a doctor or pharmacist before taking this product.

Ask a doctor before use if you have

- persistent or chronic cough such as occurs with smoking, asthma, chronic bronchitis, or emphysema
- cough accompanied by too much phlegm (mucus)

When using this product,

do not use more than directed.

Stop use and ask a doctor if

cough lasts more than 7 days, comes back, or occurs with fever, rash or persistent headache. These could be signs of a serious condition.

If pregnant or breast-feeding,

ask a health professional before use.

Keep out of reach of children.

In case of overdose, get medical help or contact a Poison Control Center (1-800-222-1222) right away.

Directions

- do not take more than 6 doses in any 24-hour period
- measure only with dosing cup provided. Do not use any other device
- keep dosing cup with product
- mL = milliliter
- dose as follows or as directed by a doctor
- adults and children 12 years of age and older: 20 mL every 4 hours
- children under 12 years of age: do not use

Other information

- each 20 mL contains: sodium 20 mg
- store between 20-25°C (68-77°F). Do not refrigerate.

Inactive ingredients

citric acid, disodium EDTA, FD&C red #40, flavor, glycerin, propyl gallate, propylene glycol, purified water, sodium benzoate, sodium citrate, sorbitol, sucralose, xanthan gum

Principal Display Panel

*Compare to the active ingredients in Maximum Strength Mucinex® Fast-Max® DM Max

MAXIMUM STRENGTH

mucus relief

DM max

dextromethorphan HBr 20 mg

guaifenesin 400 mg

cough suppressant

expectorant

controls cough

relieves chest congestion

thin & loosens mucus

4 hour dosing

for ages 12+

*This product is not manufactured or distributed by Reckitt Benckiser, distributor of Maximum Strength Mucinex® Fast-Max® DM Max

TAMPER EVIDENT: DO NOT USE IF PRINTED SAFETY SEAL UNDER CAP IS BROKEN OR MISSING.

DISTRIBUTED BY: RITE AID

30 HUNTER LANE

CAMP HILL, PA 17011

Questions or comments? Call 1-877-753-3935 Monday-Friday 9AM-5PM EST

Package Label

RITE AID Maximum Strength Mucus Relief DM Max